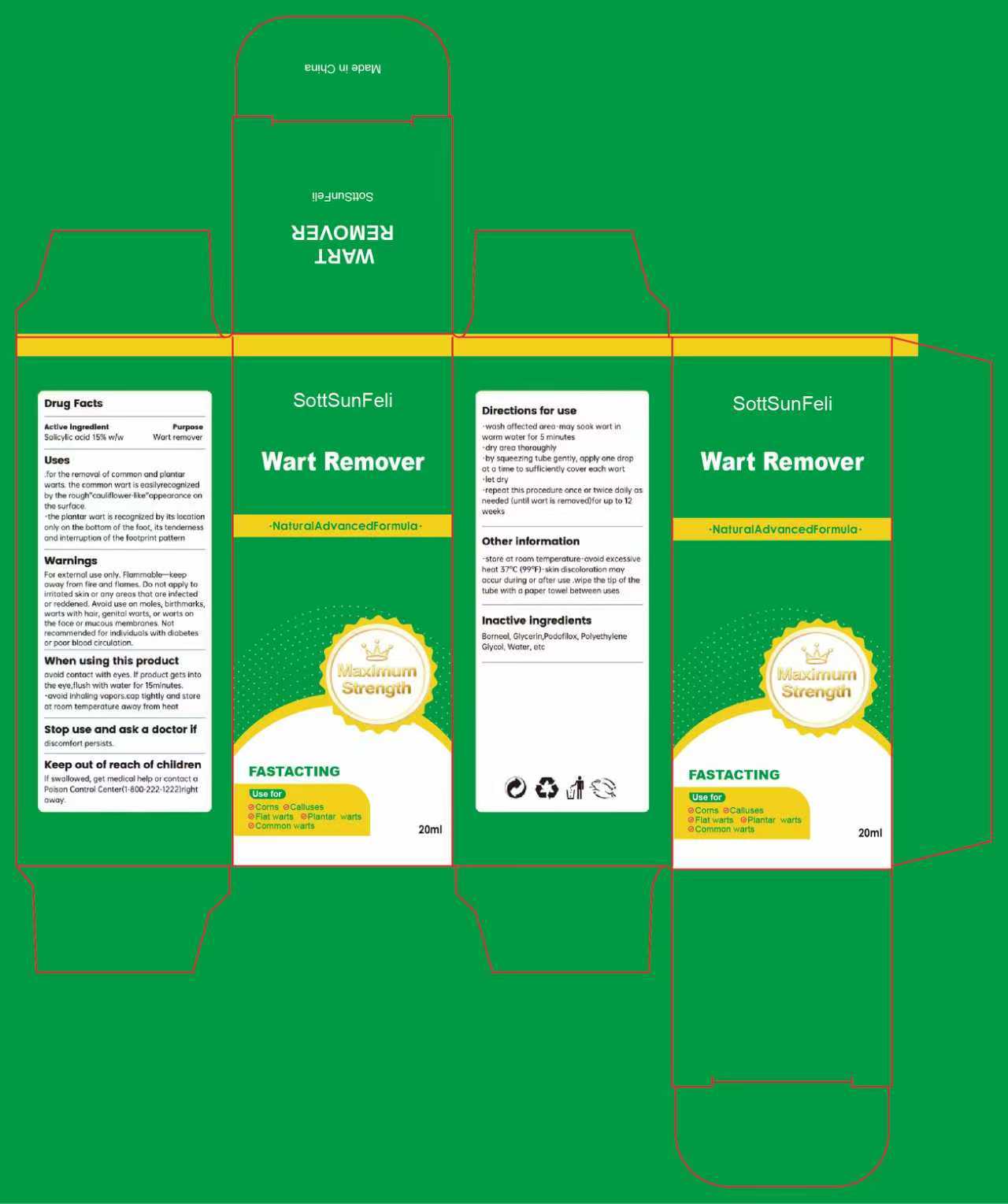 DRUG LABEL: SottSunFeli Wart Remover
NDC: 85136-010 | Form: LIQUID
Manufacturer: Henan Toudaorong Biotechnology Co., Ltd.
Category: otc | Type: HUMAN OTC DRUG LABEL
Date: 20251114

ACTIVE INGREDIENTS: SALICYLIC ACID 15 g/100 mL
INACTIVE INGREDIENTS: BORNEOL; POLYETHYLENE GLYCOL, UNSPECIFIED; WATER; GLYCERIN; PODOFILOX

ACTIVE INGREDIENT

SALICYLIC ACID

PURPOSE

for the removal of common and plantar warts

Keep out of reach of chlldren

WARNINGS

For external use only. Flammable.
Keep away from fire and flame.

INDICATIONS AND USAGE

Wash the affected area.
May soak wart in warm water for 5 minutes.

Dry area thoroughly.

Use a brush to apply a sufficient amount to cover each wart. Let it dry.

Repeat this procedure once or twice daily as needed (until wart is removed) for up to 12 weeks.

DOSAGE AND ADMINISTRATION

Wash the affected area.
May soak wart in warm water for 5 minutes.

INACTIVE INGREDIENT

BORNEOL

POLYETHYLENE GLYCOL, UNSPECIFIED

WATER

GLYCERIN

PODOFILOX